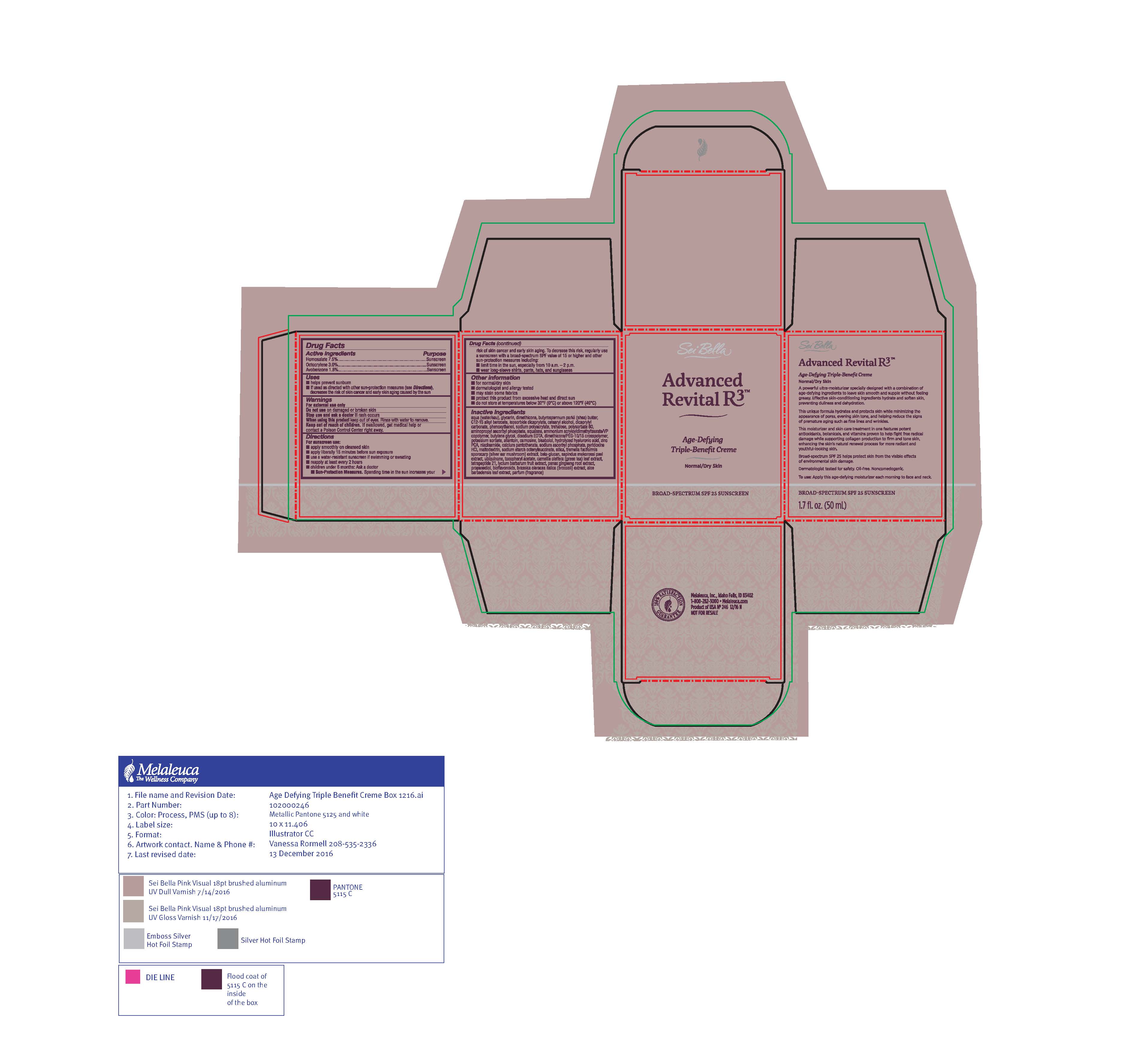 DRUG LABEL: Sei Bella
NDC: 54473-276 | Form: CREAM
Manufacturer: Melaleuca, Inc.
Category: otc | Type: HUMAN OTC DRUG LABEL
Date: 20200319

ACTIVE INGREDIENTS: AVOBENZONE 0.9 g/50 mL; HOMOSALATE 3 g/50 mL; OCTOCRYLENE 0.93 g/50 mL
INACTIVE INGREDIENTS: SODIUM ASCORBYL PHOSPHATE; PYRIDOXINE HYDROCHLORIDE; SILICON DIOXIDE; PROPANEDIOL; TETRAPEPTIDE-21; POLYSACCHARIDE-K; CALCIUM PANTOTHENATE; MALTODEXTRIN; TREMELLA FUCIFORMIS FRUITING BODY; .ALPHA.-TOCOPHEROL ACETATE; UBIDECARENONE; ASIAN GINSENG; ZINC PIDOLATE; NIACINAMIDE; ALOE VERA LEAF; BUTYLENE GLYCOL; ALKYL (C12-15) BENZOATE; CAMELLIA OLEIFERA LEAF; CETOSTEARYL ALCOHOL; DICAPRYLYL CARBONATE; TREHALOSE; DIMETHICONE; POLYSORBATE 60; GLYCERIN; AMINOPROPYL ASCORBYL PHOSPHATE; LYCIUM BARBARUM FRUIT; SQUALANE; PHENOXYETHANOL; POTASSIUM SORBATE; AMMONIUM ACRYLOYLDIMETHYLTAURATE/VP COPOLYMER; SHEA BUTTER; EDETATE DISODIUM ANHYDROUS; ALLANTOIN; CARNOSINE; .ALPHA.-BISABOLOL, (+/-)-; WATER; HYALURONIC ACID; OCTENYLSUCCINIC ACID; ISOSORBIDE DICAPRYLATE; SAPINDUS MUKOROSSI FRUIT RIND; CITRUS BIOFLAVONOIDS; BROCCOLI SPROUT

Sei Bella Advanced Revital R3 Age-Defying Creme - SPF 25 - Normal to Dry

Active ingredients
Avobenzone 1.8%, Homosalate 6%, Octisalate 3%, Octocrylane 1.86%, Oxybenzone 1.8%

Purpose
Sunscreen

Use

- provides moderate protection against sunburn

Warnings
For external use only

When using this product

- keep out of eyes. Rinse with water to remove.

Stop use and ask a doctor if

- rash or irritation develops and lasts

Keep out of reach of children. If swallowed, get medical help or contact a Poison Control Center right away.

Directions

- apply smoothly on cleansed skin before sun exposure and as needed
- children under 6 months of age: ask a doctor

Other information

- dermatologist and allergy tested

GENERAL PRECAUTIONS

- Sun alert: Limiting sun exposure, wearing protective clothing, and using sunscreens may reduce the risks of skin aging, skin cancer, and other harmful effects of the sun
- may stain some fabrics

STORAGE AND HANDLING

- do not store at temperatures below 32°F (0°C) or above 120°F (49°C)

Inactive ingredients
aqua (water/eau), polyacrylate-15, polyacrylate-17, glycerin, cetyl palmitate, C20-22 alkyl phosphate, C20-22 alcohols, butyrospermum parkii (shea butter), C12-15 alkyl benzoate, trisloxane, dimethicone, cyclopentasiloxane, dimethicone crosspolymer, C14-22 alcohols, C12-20 alkyl glucoside, propylheptyl caprylate, caprylic/capric triglycerides, acetyl tetrapeptide-9, phenoxyethanol, cetyl alcohol, xanthan gum, triethanolamine, sodium polyacrylate, potassium sorbate, trisodium ethylenediamine disuccinate, parfum, bisabolol, panax ginseng root extract, camellia oleifera leaf extract, lycium barbarum fruit extract, aloe barbadensis leaf juice, ginkgo biloba leaf extract, butylene glycol, allantoin, tocopheryl acetate, linalool, hexyl cinnamal, benzyl salicylate, alpha isomethyl ionone